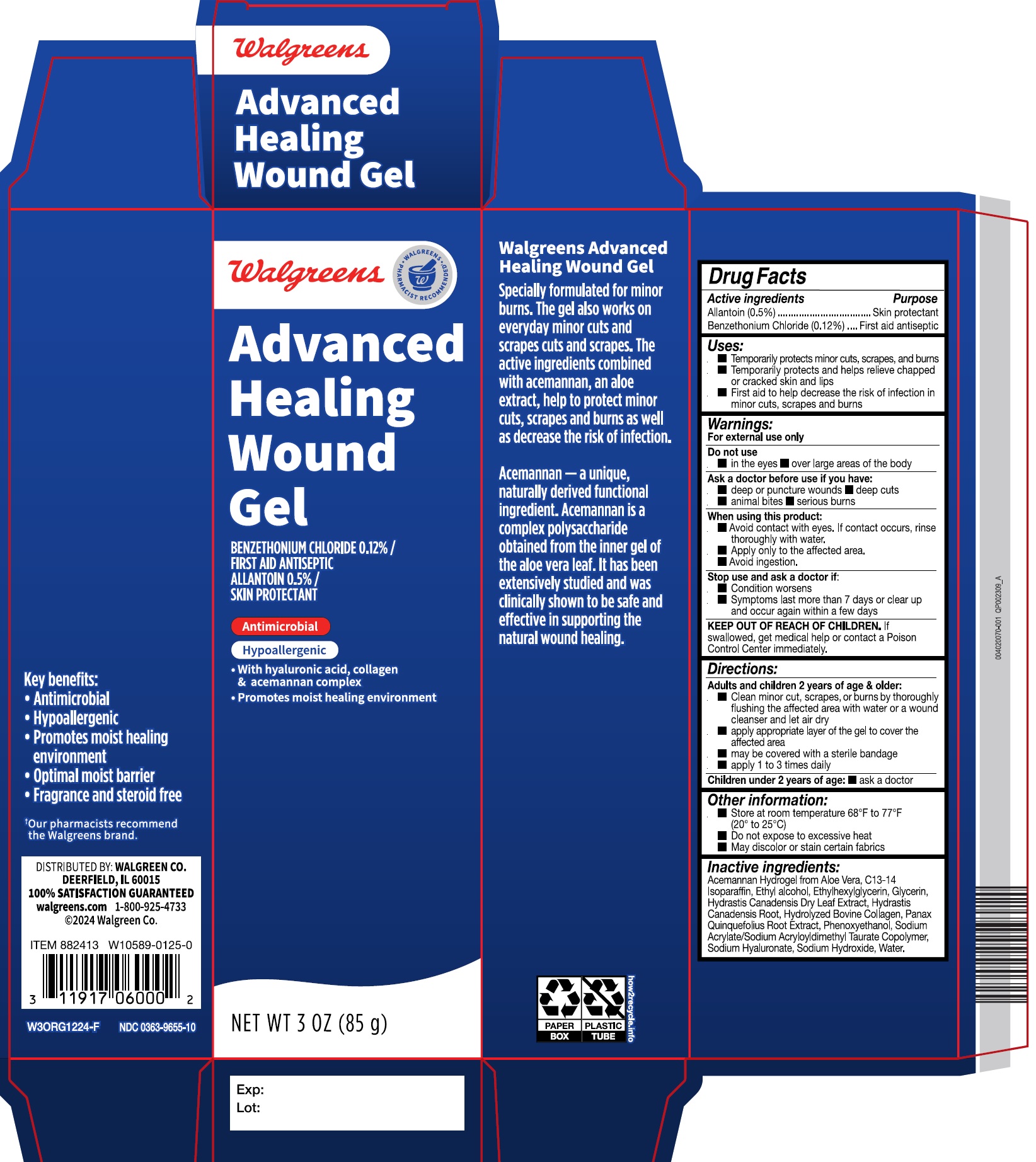 DRUG LABEL: Walgreens Advanced Wound Hydrogel
NDC: 0363-9655 | Form: GEL
Manufacturer: WALGREEN COMPANY
Category: otc | Type: HUMAN OTC DRUG LABEL
Date: 20250408

ACTIVE INGREDIENTS: BENZETHONIUM CHLORIDE 1.2 mg/1 mL; ALLANTOIN 0.5 mg/1 mL
INACTIVE INGREDIENTS: GLYCERIN; HYDRASTIS CANADENSIS WHOLE; HYDROLYZED BOVINE ELASTIN (BASE; 1000 MW); SODIUM HYALURONATE; SODIUM HYDROXIDE; WATER; ETHYLHEXYLGLYCERIN; ACEMANNAN; C13-14 ISOPARAFFIN; AMERICAN GINSENG; SODIUM ACRYLATE; PHENOXYETHANOL; ALCOHOL

Walgreens Advanced Wound Hydrogel

Active ingredients

Allantoin (0.5%)

Benzethonium Chloride (0.12%)

Uses:

Temporarily protects minor cuts, scrapes, and burns
Temporarily protects and helps relieve chapped or cracked skin and lips
First aid to help decrease the risk of infection in minor cuts, scrapes and burns

Warnings:

For external use only

Ask a doctor before use if you have:

- Deep or puncture wounds
- deep cuts
- Animal bite
- Serious burns

Do not use:

- in the eyes
- over large areas of the body

When using this product:

- Avoid contact with eyes. If contact occurs, rinse thoroughly with water.
- Apply only to the affected area.
- Avoid ingestion.

Stop use and ask a doctor if:

- Condition worsens
- Symptoms last more than 7 days or clear up and occur again within a few days

KEEP OUT OF REACH OF CHILDREN.

If swallowed, get medical help or contact a Poison Control Center immediately.

Directions:

Adults and children 2 years of age & older:

- Clean minor cut, scrapes, or burns by thoroughly flushing the affected area with water or a wound cleanser and let air dry
- apply appropriate layer of the gel to cover the affected area
- may be covered with a sterile bandage
- apply 1 to 3 times daily

Children under 2 years of age:

- ask a doctor

Other information:

- Store at room temperature 68°F -77°F (20° to 25°C)
- Do not expose to excessive heat
- May discolor or stain certain fabrics

Inactive ingredients:

Acemannan Hydrogel from Aloe Vera, C13-14 Isoparaffin, Ethyl alcohol, Ethylhexylglycerin, Glycerin, Hydrastis Canadensis Dry Leaf Extract, Hydrastis Canadensis Root, Hydrolyzed Bovine Collagen, Panax Quinquefolius Root Extract, Phenoxyethanol, Sodium Acrylate/Sodium Acryloyldimethyl Taurate Copolymer, Sodium Hyaluronate, Sodium Hydroxide, Water.